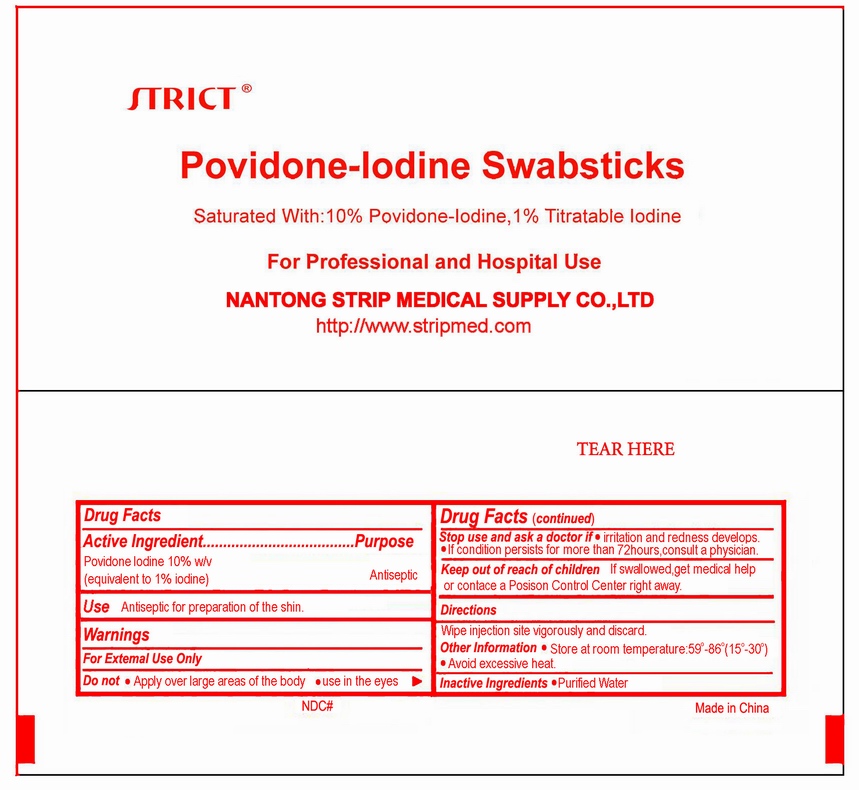 DRUG LABEL: Povidone-Iodine
NDC: 35617-397 | Form: SWAB
Manufacturer: NANTONG STRIP MEDICAL SUPPLY CO.,LTD. 
Category: otc | Type: HUMAN OTC DRUG LABEL
Date: 20110705

ACTIVE INGREDIENTS: POVIDONE-IODINE 0.1 mL/1 1
INACTIVE INGREDIENTS: WATER 0.9 mL/1 1

Drug Fact Povidone-Iodine Swabsticks

Use

Antiseptic for preparation of skin.

Purpose

Antiseptic

Cautions

For External Use Only.
Do not use:
Apply over large areas of the body, use in the eyes
Drug Facts (continued):
Stop use and ask a doctor if irritation and redness develops.
If condition persists for more than 72 hours, consult a physician.

Keep out of reach of children.
If swallowed, get medical help or contact a Poison Control Center right away.

Directions

Wipe injection site vigorously and discard.

Other information

Store at room temperature, 59º-86ºF(15º-30℃), avoid excessive heat.

Active Ingredient

Povidone Iodine 10% w/v (equivalent to 1%iodine)

Inactive Ingredients

Water

PACKAGE LABEL

Enter section text here